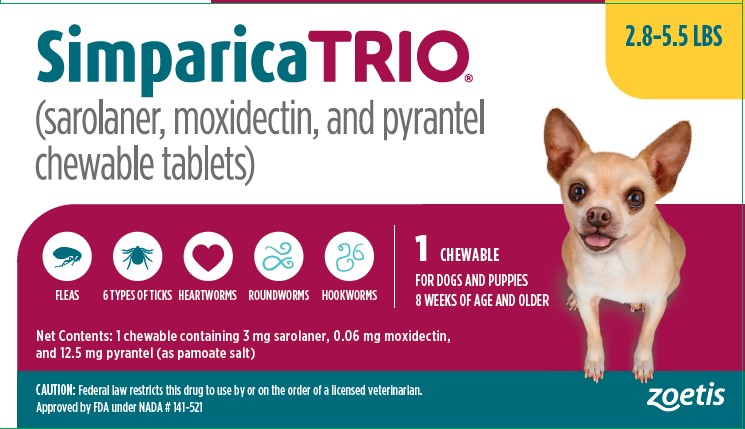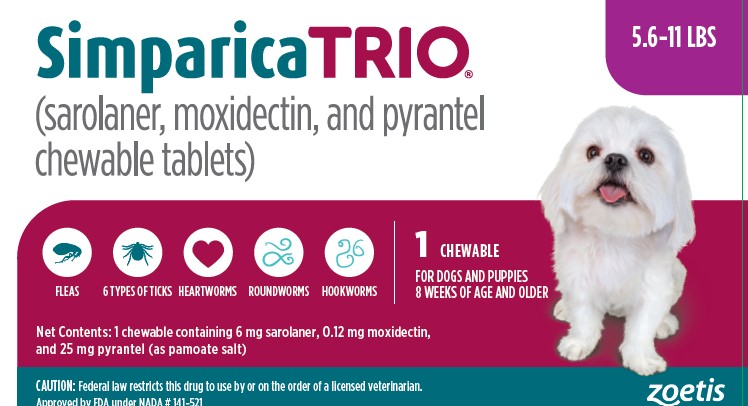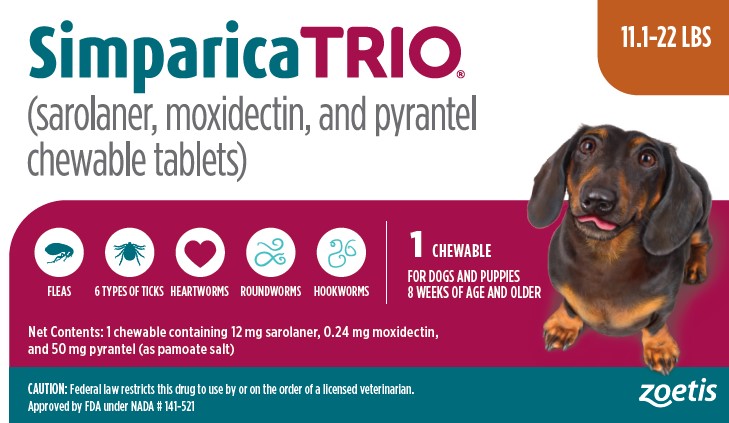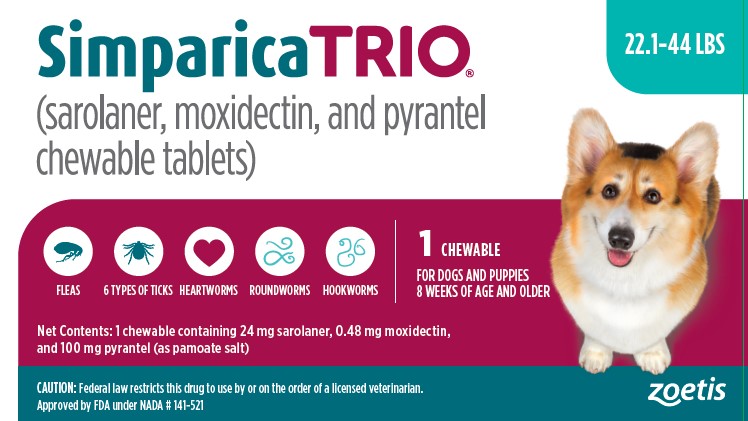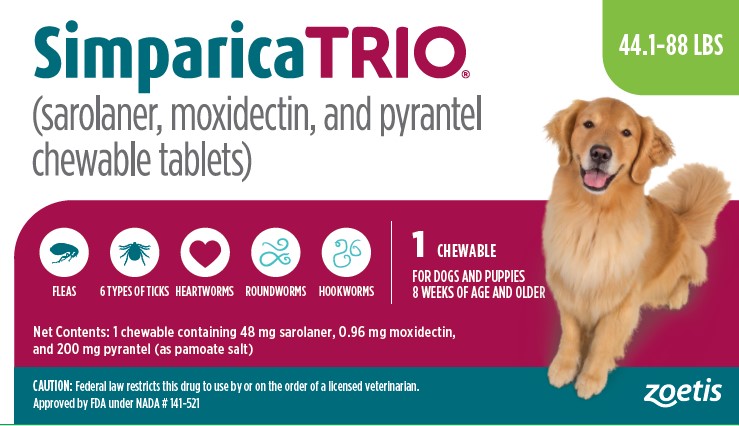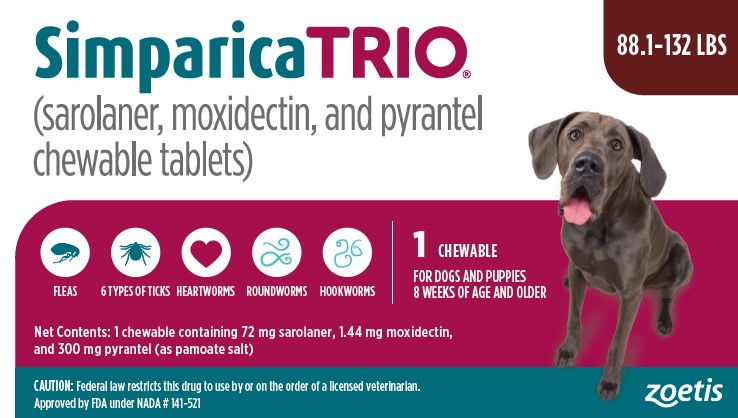 DRUG LABEL: Simparica TRIO
NDC: 54771-2667 | Form: TABLET, CHEWABLE
Manufacturer: Zoetis Inc.
Category: animal | Type: PRESCRIPTION ANIMAL DRUG LABEL
Date: 20250523

ACTIVE INGREDIENTS: SAROLANER 3 mg/1 1; MOXIDECTIN .06 mg/1 1; PYRANTEL PAMOATE 12.5 mg/1 1

Simparica TRIO®

Simparica TRIO®

(sarolaner, moxidectin, and pyrantel chewable tablets)

FOR ORAL USE IN DOGS ONLY

CAUTION

Federal (USA) law restricts this drug to use by or on the order of a licensed veterinarian.

DESCRIPTION

SIMPARICA TRIO (sarolaner, moxidectin, and pyrantel chewable tablets) is a flavored, chewable tablet for administration to dogs 8 weeks of age and older. Each tablet is formulated to provide minimum dosages of 0.54 mg/lb (1.2 mg/kg) sarolaner, 0.011 mg/lb (24 μg/kg) moxidectin, and 2.27 mg/lb (5 mg/kg) pyrantel (as pamoate salt).

Sarolaner is a member of the isoxazoline class of parasiticides and the chemical name is 1‑(5’-((5S)-5-(3,5-Dichloro-4-fluorophenyl)-5-trifluoromethyl)-4,5-dihydroisoxazol-3-yl)-3’-H-spiro(azetidine-3,1’-(2)benzofuran)-1-yl)-2-(methylsulfonyl)ethanone. SIMPARICA TRIO contains the S-enantiomer of sarolaner.

Moxidectin is a semi-synthetic methoxime derivative of nemadectin which is a fermentation product of Streptomyces cyaneogriseus subspecies noncyanogenus. Moxidectin is a pentacyclic 16-membered lactone macrolide. The chemical name for moxidectin is (6R,23E,25S)-5-O-Demethyl-28-deoxy-25-[(1E)-1,3-dimethyl-1-buten-1-yl]-6,28-epoxy-23-(methoxyimino)milbemycin B.

Pyrantel belongs to a family classified chemically as tetrahydropyrimidines and the chemical name is (E)‑1,4,5,6-Tetrahydro-1-methyl-2-[2-(2-thienyl) vinyl] pyrimidine 4,4’ methylenebis [3-hydroxy-2-naphthoate] (1:1). It is a yellow, water-insoluble crystalline salt of the tetrahydropyrimidine base and pamoic acid containing 34.7% base activity.

INDICATIONS

SIMPARICA TRIO is indicated for the prevention of heartworm disease caused by Dirofilaria immitis and for the treatment and control of roundworm (immature adult and adult Toxocara canis and adult Toxascaris leonina) and hookworm (L4, immature adult, and adult Ancylostoma caninum and adult Uncinaria stenocephala) infections. SIMPARICA TRIO kills adult fleas (Ctenocephalides felis) and is indicated for the treatment and prevention of flea infestations, the prevention of Dipylidium caninum (tapeworm) infections as a direct result of killing Ctenocephalides felis vector fleas on the treated dog, and the treatment and control of tick infestations with Amblyomma americanum (lone star tick), Amblyommamaculatum (Gulf Coast tick), Dermacentor variabilis (American dog tick), Ixodes scapularis (black-legged tick), Rhipicephalus sanguineus (brown dog tick), and Haemaphysalis longicornis (Asian longhorned tick) for one month in dogs and puppies 8 weeks of age and older, and weighing 2.8 pounds or greater. SIMPARICA TRIO is indicated for the prevention of Borrelia burgdorferi infections as a direct result of killing Ixodes scapularis vector ticks.

DOSAGE AND ADMINISTRATION

SIMPARICA TRIO is given orally once a month, at the recommended minimum dose of 0.54 mg/lb (1.2 mg/kg) sarolaner, 0.011 mg/lb (24 μg/kg) moxidectin, and 2.27 mg/lb (5 mg/kg) pyrantel (as pamoate salt).

Dosage Schedule

Body Weight (lbs) | Sarolaner per Tablet (mg) | Moxidectin per Tablet (mg) | Pyrantel per Tablet (mg) | Number of Tablets Administered
2.8 to 5.5 | 3 | 0.06 | 12.5 | One
5.6 to 11.0 | 6 | 0.12 | 25 | One
11.1 to 22.0 | 12 | 0.24 | 50 | One
22.1 to 44.0 | 24 | 0.48 | 100 | One
44.1 to 88.0 | 48 | 0.96 | 200 | One
88.1 to 132.0 | 72 | 1.44 | 300 | One
>132.0 | Administer the appropriate combination of tablets

SIMPARICA TRIO can be offered to the dog with or without food.
Care should be taken to ensure that the dog consumes the complete dose and that part of the dose is not lost or refused. If a dose is missed, give SIMPARICA TRIO immediately and resume monthly dosing.

Heartworm Prevention:
SIMPARICA TRIO should be administered at monthly intervals year‑round or at least within one month of the animal’s first seasonal exposure to mosquitoes and continuing until at least 1 month after the dog’s last seasonal exposure. If a dose is missed, give SIMPARICA TRIO immediately and resume monthly dosing. When replacing a monthly heartworm preventive product, SIMPARICA TRIO should be given within one month of the last dose of the former medication.

Flea Treatment and Prevention:
Treatment with SIMPARICA TRIO may begin at any time of the year. SIMPARICA TRIO should be administered year‑round at monthly intervals or started at least one month before fleas become active.
To minimize the likelihood of flea re‑infestation, it is important to treat all dogs and cats within a household with a flea control product.
Tapeworm Prevention:
Treatment with SIMPARICA TRIO may begin at any time of the year. SIMPARICA TRIO should be administered year-round at monthly intervals or started at least one month before fleas become active.
SIMPARICA TRIO will only prevent D. caninum infections by killing the fleas on the treated dog. Dogs may also become infected with D. caninum by ingesting fleas from untreated animals, it is therefore recommended that all pets in a household are treated for fleas.

Tick Treatment and Control:
Treatment with SIMPARICA TRIO can begin at any time of the year. SIMPARICA TRIO should be administered year‑round at monthly intervals or started at least one month before ticks become active.

Intestinal Nematode Treatment and Control:
For the treatment of roundworm (immature adult and adult Toxocara canis and adult Toxascaris leonina) and hookworm (L4, immature adult, and adult Ancylostoma caninum and adult Uncinaria stenocephala) infections, SIMPARICA TRIO should be administered once as a single dose. Monthly use of SIMPARICA TRIO will control any subsequent infections.

CONTRAINDICATIONS

There are no known contraindications for the use of SIMPARICA TRIO.

WARNINGS

Not for use in humans. Keep this and all drugs out of reach of children.
Keep SIMPARICA TRIO in a secure location out of reach of dogs, cats and other animals to prevent accidental ingestion or overdose.

PRECAUTIONS

Sarolaner, one of the ingredients in SIMPARICA TRIO, is a member of the isoxazoline class. This class has been associated with neurologic adverse reactions including tremors, ataxia, and seizures. Seizures have been reported in dogs receiving isoxazoline class drugs, even in dogs without a history of seizures. Use with caution in dogs with a history of seizures or neurologic disorders.

Prior to administration of SIMPARICA TRIO, dogs should be tested for existing heartworm infections. Infected dogs should be treated with an adulticide to remove adult heartworms. SIMPARICA TRIO is not effective against adult D. immitis.

The safe use of SIMPARICA TRIO has not been evaluated in breeding, pregnant, or lactating dogs.

ADVERSE REACTIONS

In a field safety and effectiveness study, SIMPARICA TRIO was administered to dogs for the prevention of heartworm disease. The study included a total of 410 dogs treated once monthly for 11 treatments (272 treated with SIMPARICA TRIO and 138 treated with an active control). Over the 330-day study period, all observations of potential adverse reactions were recorded. The most frequent reactions reported in the SIMPARICA TRIO group are presented in the following table.

Table 1. Dogs with Adverse Reactions

Clinical Sign | SIMPARICA TRIO n = 272 | Active Control n = 138
Vomiting | 14.3% | 10.9%
Diarrhea | 13.2% | 8.0%
Lethargy | 8.5% | 6.5%
Anorexia | 5.1% | 5.8%
Polyuria | 3.7% | 3.6%
Hyperactivity | 2.2% | 0.7%
Polydipsia | 2.2% | 2.9%

In a second field safety and effectiveness study, SIMPARICA TRIO was administered to 278 dogs with fleas. Adverse reactions in dogs treated with SIMPARICA TRIO included diarrhea.
In a third field safety and effectiveness study, SIMPARICA TRIO was administered to 120 dogs with roundworms. Adverse reactions in dogs treated with SIMPARICA TRIO included diarrhea and vomiting.

In one well-controlled laboratory study, one dog had a seizure 16 days after administration of SIMPARICA TRIO.

Post-Approval Experience (2024)

The following adverse events are based on post-approval adverse drug experience reporting for SIMPARICA TRIO. Not all adverse events are reported to FDA/CVM. It is not always possible to reliably estimate the adverse event frequency or establish a causal relationship to product exposure using these data.
The following adverse events reported in dogs are listed in decreasing order of reporting frequency:
Vomiting, diarrhea (with and without blood), seizure, lethargy, anorexia, muscle tremor, ataxia, non-specific behavioral changes, and pruritus.

CONTACT INFORMATION

For a copy of the Safety Data Sheet or to report adverse reactions, call Zoetis Inc. at 1-888-963-8471. For additional information about adverse drug experience reporting for animal drugs, contact FDA at 1-888-FDA-VETS or www.fda.gov/reportanimalae.

CLINICAL PHARMACOLOGY

Following oral administration of SIMPARICA TRIO in Beagle dogs (13 to 15 months of age at the time of initial dosing), sarolaner and moxidectin were rapidly and well-absorbed. Following a single oral dose of SIMPARICA TRIO (sarolaner dose of 1.2 mg/kg), the sarolaner mean maximum plasma concentration (Cmax) was 523 ng/mL with a mean time to maximum concentration (Tmax) of 3.5 hours and an absolute bioavailability of 88%. At a moxidectin dose of 0.024 mg/kg, the moxidectin mean Cmax was 13.1 ng/mL with a mean Tmax of 2.4 hours and an absolute bioavailability of 67%.

Following intravenous (IV) dosing of a combination solution of sarolaner and moxidectin, the sarolaner volume of distribution (Vss) was 2.4 L/kg and systemic clearance (CL) was 6.0 mL/kg/hr. For moxidectin the Vss was 7.65 L/kg and CL was 26.6 mL/kg/hr. The terminal half‑lives were similar after oral and IV dosing for both sarolaner (12 days) and moxidectin (11 days). The primary route of elimination of both sarolaner and moxidectin is biliary excretion with minimal metabolism.

Following an oral dose of SIMPARICA TRIO containing 5 mg/kg pyrantel (as pamoate salt), pyrantel has measurable plasma concentrations, but they are low and highly variable. Pyrantel pamoate is intended to remain in the gastrointestinal tract allowing for delivery of effective concentrations to gastrointestinal nematodes.

MODE OF ACTION

SIMPARICA TRIO contains three active pharmaceutical ingredients, sarolaner, moxidectin, and pyrantel pamoate.

Sarolaner is an acaricide and insecticide belonging to the isoxazoline group. Sarolaner inhibits the function of the neurotransmitter gamma aminobutyric acid (GABA) receptor and glutamate receptor, and works at the neuromuscular junction in insects. This results in uncontrolled neuromuscular activity leading to death in insects or acarines.

Moxidectin is an endectocide in the macrocyclic lactone class. Moxidectin acts by interfering with the chloride channel‑mediated neurotransmission in the parasite. This results in paralysis and death of the parasite.

Pyrantel pamoate is a nematocide belonging to the tetrahydropyrimidine class. Pyrantel acts as a depolarizing, neuromuscular‑blocking agent in susceptible parasites, which causes paralysis and death or expulsion of the organism.

EFFECTIVENESS

Heartworm Prevention
In two well‑controlled laboratory studies, a single oral dose of SIMPARICA TRIO was 100% effective in preventing the development of adult D. immitis in dogs inoculated with infective larvae 30 days before treatment.
In a well-controlled US field study consisting of 246 dogs administered SIMPARICA TRIO and 119 administered an active control, no dogs treated with SIMPARICA TRIO tested positive for heartworm disease. All dogs treated with SIMPARICA TRIO were negative for D. immitis antigen and blood microfilariae at study completion on day 330.
Flea Treatment and Prevention
In a well‑controlled laboratory study, SIMPARICA TRIO began to kill fleas at 4 hours and demonstrated 100% effectiveness at 8 hours after initial administration. After weekly re‑infestations, SIMPARICA TRIO reduced the number of live fleas by ≥97.8% within 12 hours of infestation for 28 days.
In a separate well‑controlled laboratory study, SIMPARICA TRIO demonstrated 100% effectiveness against adult fleas within 24 hours following treatment and maintained ≥99.7% effectiveness against weekly re‑infestations for 35 days.
In a study to explore flea egg production and viability, SIMPARICA TRIO killed fleas before they could lay eggs for 35 days.
In a well‑controlled 60‑day US field study conducted in dogs with existing flea infestations of varying severity, the effectiveness of SIMPARICA TRIO against fleas on Day 30 and 60 visits was 99.0% and 99.7%, respectively, compared to baseline. Dogs with signs of flea allergy dermatitis showed improvement in erythema, papules, scaling, alopecia, dermatitis/pyodermatitis and pruritus as a direct result of eliminating fleas.

Tapeworm Prevention
In two well-controlled laboratory studies, a single oral dose of SIMPARICA TRIO was ≥ 92.1% effective in preventing Dipylidium caninum infections in dogs after multiple infestations with Dipylidium caninum-infected C. felis fleas for one month.
Tick Treatment and Control
In a well‑controlled laboratory study, SIMPARICA TRIO began to kill existing I. scapularis within 8 hours, SIMPARICA TRIO reduced the number of live ticks by ≥94.2% within 24 hours of infestation for 28 days.
In well-controlled laboratory studies, SIMPARICA TRIO demonstrated ≥98.9% effectiveness against an existing infestation of Amblyomma maculatum, Ixodes scapularis, Rhipicephalus sanguineus, Dermacentor variabilis, and Haemaphysalis longicornis 48 hours post-administration and maintained ≥90.4% effectiveness 48 hours after re-infestation for at least 28 days. Against Amblyomma americanum, SIMPARICA TRIO demonstrated ≥99.4% effectiveness 72 hours after treatment of existing infestations, and maintained ≥98.4% effectiveness 72 hours after re‑infestation for at least 28 days. In two separate, well-controlled laboratory studies, SIMPARICA TRIO was effective at preventing Borrelia burgdorferi infections after dogs were infested with Ixodes scapularis vector ticks 28 days post-treatment.
Intestinal Nematode Treatment and Control
Elimination of roundworms (immature adult and adult Toxocara canis and adult Toxascaris leonina) and hookworm (L4, immature adult, and adult Ancylostoma caninum and adult Uncinaria stenocephala) was demonstrated in well‑controlled laboratory studies.
In a 10-day multi‑center field study, SIMPARICA TRIO was effective against Toxocara canis and reduced fecal egg counts 99.2%.

ANIMAL SAFETY

Margin of Safety: SIMPARICA TRIO was administered orally to 8‑week‑old Beagle puppies at doses of 1, 3, and 5X the maximum labeled dose (2.4 mg/kg sarolaner, 48 μg/kg moxidectin, and 10 mg/kg pyrantel) at 28 day intervals for 7 treatments. Dogs in the control group received placebo. There were no clinically‑relevant, treatment related effects on clinical observations, body weights, food consumption, clinical pathology (hematology, coagulation, serum chemistry, and urinalysis), gross pathology, histopathology, or organ weights. During the end-of-study ophthalmic examination, the following change was found: one 1X dog had retinal dysplasia (OS folds).

Ivermectin-sensitive Collie Safety:
SIMPARICA TRIO was administered orally once at 1, 3 and 5X the maximum labeled dose to Collies that had been pre‑screened for avermectin sensitivity. Dogs in the control group received placebo. Clinical signs (ataxia, muscle fasciculations, mydriasis) associated with avermectin sensitivity were observed in the 5X group. All dogs were completely recovered by the third day of the study.

Heartworm-Positive Safety:
SIMPARICA TRIO was administered orally at 1 and 3X the maximum labeled dose at 28 day intervals for 3 treatments to Beagle dogs with patent adult heartworm infections and circulating microfilariae. Dogs in the control group received placebo. Diarrhea occurred more commonly in the treated dogs and also more often in the 3X group compared with the 1X group. Two dogs (1 each in 1X and 3X) developed a fever less than 24 hours after the first dose. The fever may have been a transient reaction to a rapid microfilaria reduction. Both dogs recovered without treatment.

Field Safety: In three well‑controlled field studies, SIMPARICA TRIO was used concurrently with other medications such as vaccines, antimicrobials, anthelmintics, antiprotozoals, steroidal and non‑steroidal anti‑inflammatory agents, anesthetic agents and analgesics. No adverse reactions were associated with the concurrent use of SIMPARICA TRIO and other medications.

STORAGE CONDITIONS

Store at or below 30°C (86°F).

HOW SUPPLIED

SIMPARICA TRIO (sarolaner, moxidectin, and pyrantel chewable tablets) is available in six flavored tablet sizes (see DOSAGE AND ADMINISTRATION). Each tablet size is available in packages of one, three, or six tablets.

Approved by FDA under NADA # 141‑521
zoetis
Distributed by:
Zoetis Inc.
Kalamazoo, MI 49007
Revised: October 2024
40050385

PRINCIPAL DISPLAY PANEL - 2.8-5.5lbs Carton

2.8-5.5lbs 52055900

PRINCIPAL DISPLAY PANEL - 5.6-11lbs Carton

5.6-11lbs 52055600

PRINCIPAL DISPLAY PANEL - 11.1-22lbs Carton

11.1-22lbs 52055100

PRINCIPAL DISPLAY PANEL - 22.1-44lbs Carton

22.1-44lbs 52054400

PRINCIPAL DISPLAY PANEL - 44.1-88lbs Carton

44.1-88lbs 52057000

PRINCIPAL DISPLAY PANEL - 88.1-132lbs Carton

88.1-132lbs 52056700